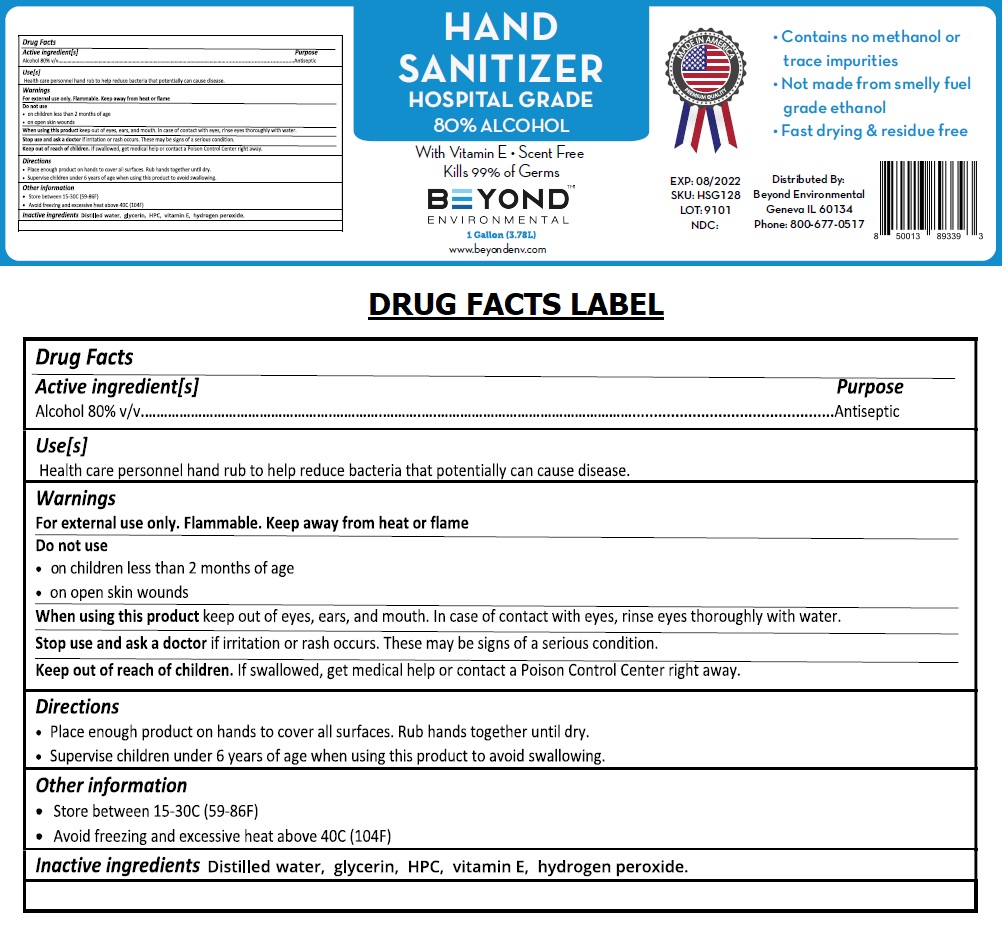 DRUG LABEL: hand sanitizer hospital grade
NDC: 79905-800 | Form: GEL
Manufacturer: Beyond Environmental, Llc
Category: otc | Type: HUMAN OTC DRUG LABEL
Date: 20200814

ACTIVE INGREDIENTS: ALCOHOL 80 L/100 L
INACTIVE INGREDIENTS: WATER; GLYCERIN; HYDROXYPROPYL CELLULOSE, UNSPECIFIED; .ALPHA.-TOCOPHEROL; HYDROGEN PEROXIDE

BEYOND ENVIRONMENTAL HAND SANITIZER

Active ingredient[s]

Alcohol 80% v/v

Purpose

Antiseptic

Use[s]

Health care personnel hand rub to help reduce bacteria that potentially can cause disease.

Warnings

For external use only. Flammable, Keep away from heat or flame

Do not use

• on children less than 2 months of age

• on open skin wounds

When using this product keep out of eyes, ears, and mouth. In case of contact with eyes, rinse eyes thoroughly with water.

Stop use and ask a doctor if irritation or rash occurs. These may be signs of a serious condition.

Keep out of reach of children. If swallowed, get medical help or contact a Poison Control Center right away.

Directions

• Place enough product on hands to cover all surfaces. Rub hands together until dry.

• Supervise children under 6 years of age when using this product to avoid swallowing.

Other information

• Store between 15-30C (59-86F)

• Avoid freezing and excessive heat above 40C (104F)

INACTIVE INGREDIENT

Inactive ingredients Distilled water, glycerin, HPC, vitamin E, hydrogen peroxide.

With Vitamin E • Scent Free

Kills 99% of Germs

• Contains no methanol or trace impurities

• Not made from smelly fuel grade ethanol

• Fast drying & residue free

www.beyondenv.com

MADE IN AMERICA

PREMIUM QUALITY

Distributed By:

Beyond Environmental

Geneva IL 60134

Phone: 800-677- 0517